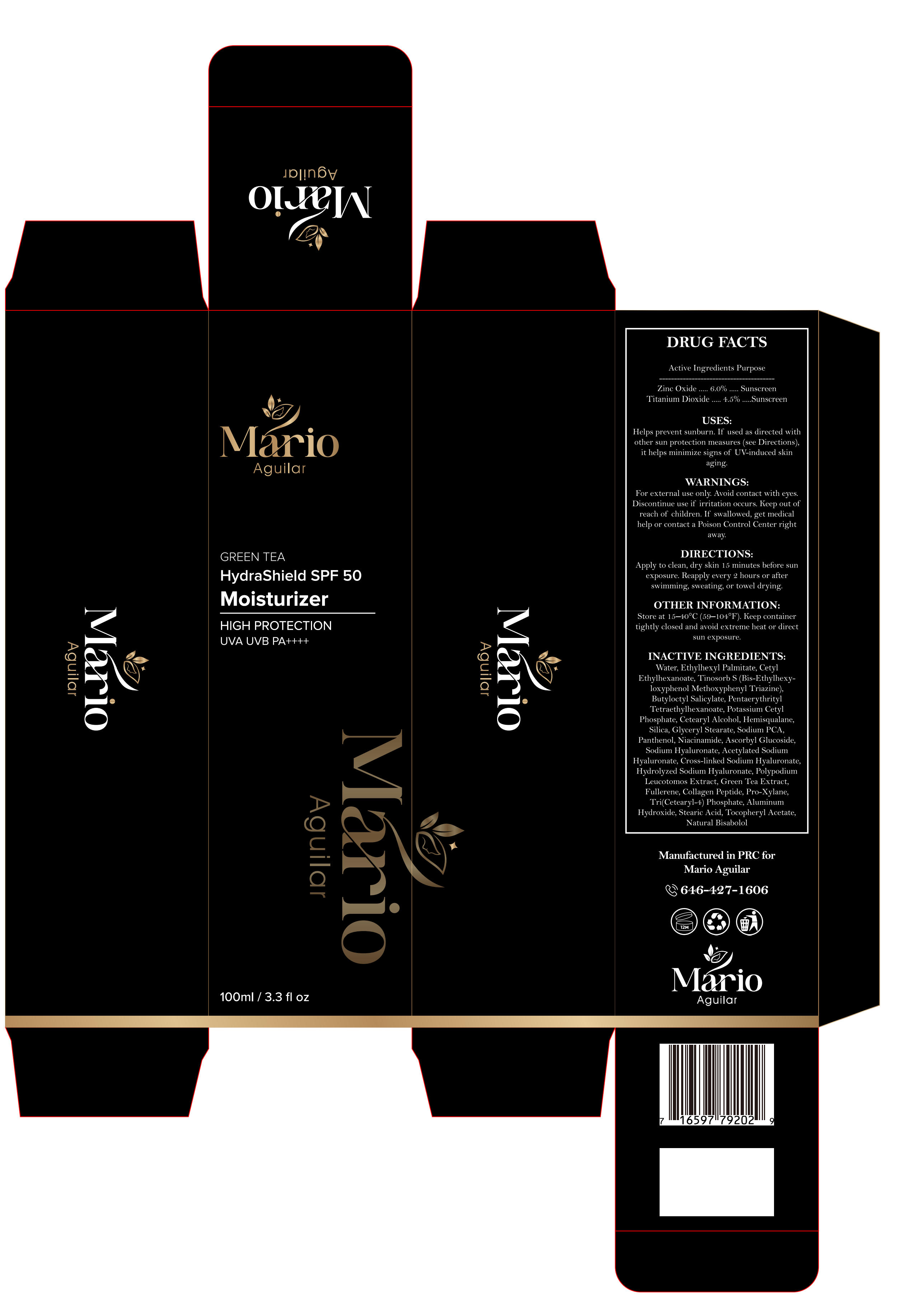 DRUG LABEL: Sandra Plasencia Dendrobium Officinale Soothing Biofermented Mask
NDC: 87036-025 | Form: LIQUID
Manufacturer: Guangzhou Meijiao Medical Biotechnology Co., Ltd.
Category: otc | Type: HUMAN OTC DRUG LABEL
Date: 20251103

ACTIVE INGREDIENTS: TITANIUM DIOXIDE 4.5 g/100 mL; ZINC OXIDE 6 g/100 mL
INACTIVE INGREDIENTS: SODIUM PCA; GLYCERYL STEARATE; ALUMINUM HYDROXIDE; SODIUM HYALURONATE; FULLERENES; STEARIC ACID; PANTHENOL; SODIUM ACETYLATED HYALURONATE; CETEARYL ALCOHOL; BISABOLOL; PENTAERYTHRITYL TETRAETHYLHEXANOATE; GREEN TEA LEAF; ASCORBYL GLUCOSIDE; POTASSIUM CETYL PHOSPHATE; BIS-ETHYLHEXYLOXYPHENOL METHOXYPHENYL TRIAZINE; NIACINAMIDE; WATER; ETHYLHEXYL PALMITATE; CETYL ETHYLHEXANOATE; BUTYLOCTYL SALICYLATE

Active Ingredients Purpose
Zinc Oxide . 6.0% … .SunscreenTitanium Dioxide .... 4.5%sunscreen

INACTIVE INGREDIENT

INACTIVE INGREDIENTS:Water, Ethylhexyl Palmitate, CetylEthylhexanoate, Tinosorb S(Bis-Ethylhexyloxyphenol Methoxyphenyl Triazine)Butyloctyl Salicylate, PentaerythritylTetraethylhexanoate, Potassium CetylPhosphate, Cetearyl Alcohol, Hemisqualane,Silica, Glyceryl Stearate, Sodium PCA,Panthenol, Niacinamide, Ascorbyl Glucoside,Sodium Hyaluronate, Acetylated SodiumHyaluronate, Cross-linked Sodium Hyaluronate,Hydrolyzed Sodium Hyaluronate, PolypodiumLeucotomos Extract, Green Tea Extract,Fullerene, Collagen Peptide, Pro-Xylane,Tri(Cetearyl-4) Phosphate, AluminumHydroxide, Stearic Acid, Tocopheryl Acetate,
Natural Bisabolol

PURPOSE

HIGH PROTECTION
UVA UVB PA++++

WARNINGS:
For external use only. Avoid contact with eyes.Discontinue use if irritation occurs. keep out ofreach of children. If swallowed, get medicalhelp or contact a Poison Control Center right
away.

WARNINGS:
For external use only. Avoid contact with eyes.Discontinue use if irritation occurs. keep out ofreach of children. If swallowed, get medicalhelp or contact a Poison Control Center right
away.

WARNINGS:
For external use only. Avoid contact with eyes.Discontinue use if irritation occurs. keep out ofreach of children. If swallowed, get medicalhelp or contact a Poison Control Center right
away.

WARNINGS:
For external use only. Avoid contact with eyes.Discontinue use if irritation occurs. keep out ofreach of children. If swallowed, get medicalhelp or contact a Poison Control Center right
away.

USES:
Helps prevent sunburn. If used as directed withother sun protection measures (see Directions)it helps minimize signs of UVinduced skin
agig.

USES:
Helps prevent sunburn. If used as directed withother sun protection measures (see Directions)it helps minimize signs of UVinduced skin
agig.

USES:
Helps prevent sunburn. If used as directed withother sun protection measures (see Directions)it helps minimize signs of UVinduced skin
agig.

PACKAGE LABEL

GREEN TEAHydraShield SPF 50MoisturizerHIGH PROTECTIONUVA UVB PA++++
DRUG FACTTS
Active Ingredients Purpose
Zinc Oxide .. 6.0% . SunscreenTitanium Dioxide . 4.5%.Sunscreen
USES:
Helps prevent sunburn, If used as directed withother sun protection measures (see Directions),it helps minimize signs of UV-induced skin
aging
WARNINGS:
For external use only. Avoid contact with eyes.Discontinue use if irritation occurs. Keep out ofreach of children. If swallowed, get medicalhelp or contact a Poison Control Center right
away
OTHER INFORMATIONStore at 15-40°C(59-104°F).Keep containertightly closed and avoid extreme heat or directsun exposure.
INACTIVE INGREDIENTS:
Water, Ethylhexyl Palmitate, CetylEthylhexanoate, Tinosorb S (Bis-Ethylhexyloxyphenol Methoxyphenyl Triazine),Butyloctyl Salicylate, PentaerythritylTetraethylhexanoate, Potassium Cetyl
Phosphate, Cetearyl Alcohol, Hemisqualane,Silica, Glyceryl Stearate, Sodium PCA,Panthenol, Niacinamide, Ascorbyl Glucoside,Sodium Hyaluronate, Acetylated SodiumHyaluronate, Cross-linked Sodium Hyaluronate,Hydrolyzed Sodium Hyaluronate, PolypodiumLeucotomos Extract, Green Tea Extract,Fullerene, Collagen Peptide, Pro-Xylane,Tri(Cetearyl-4)Phosphate, AluminumHydroxide, Stearic Acid, Tocopheryl Acetate,
Natural Bisabolol